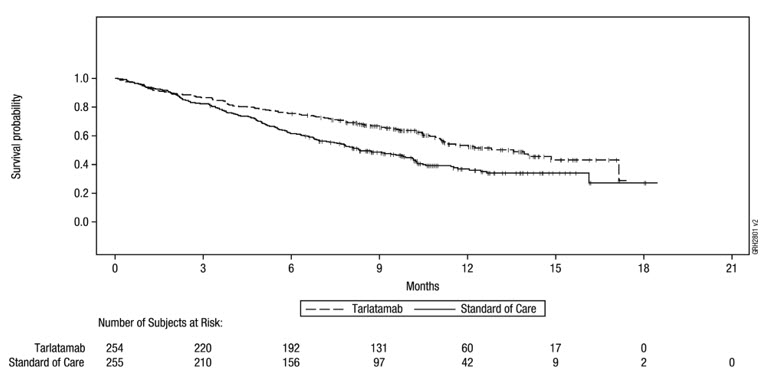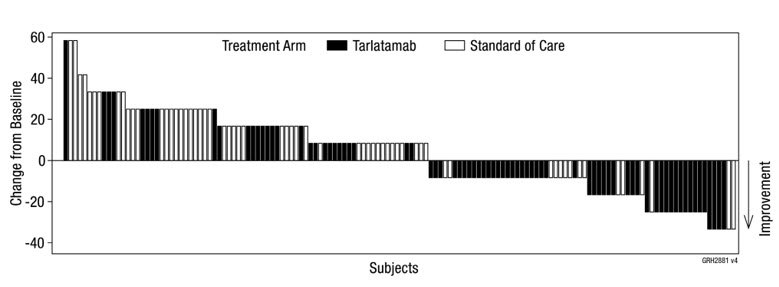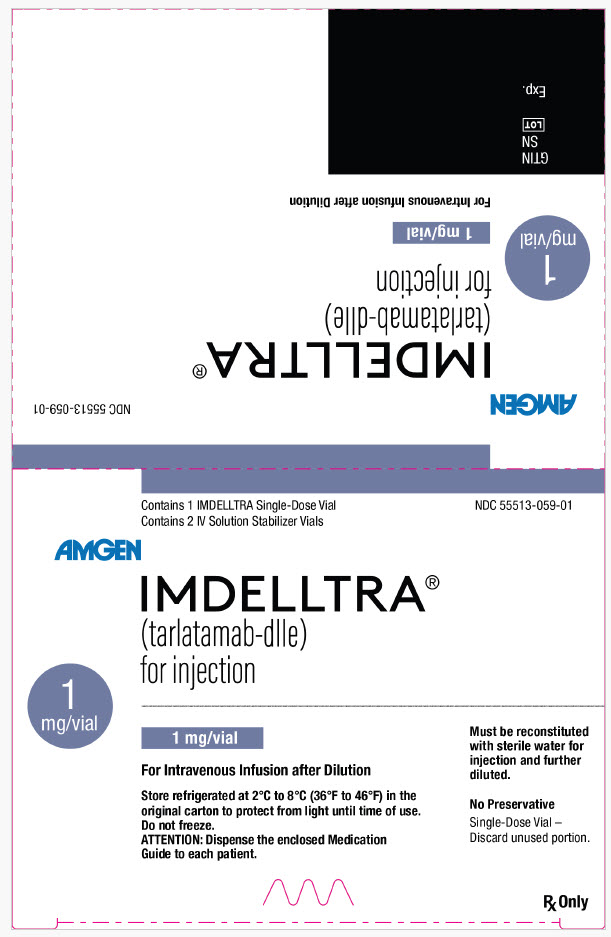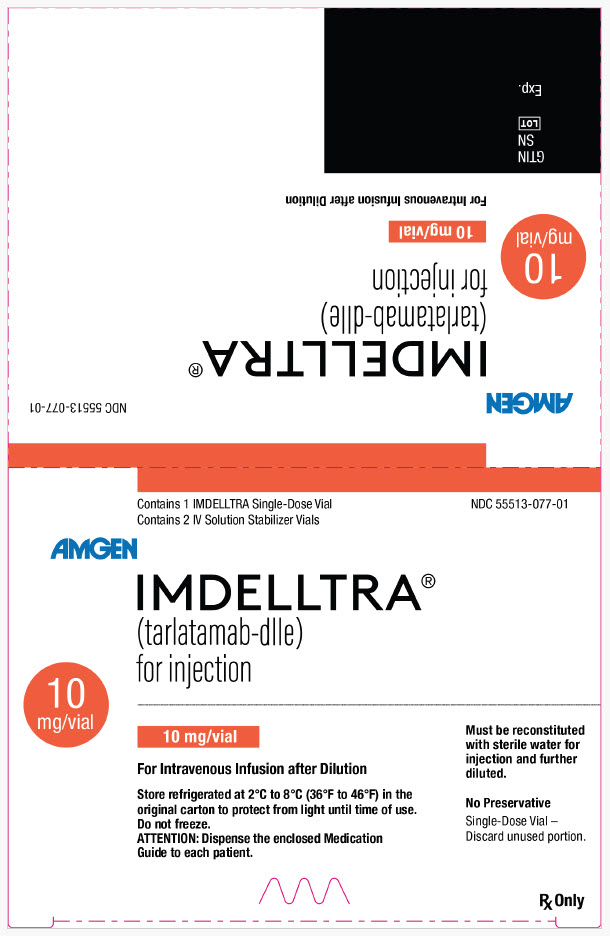 DRUG LABEL: IMDELLTRA (AMG757)
NDC: 55513-059 | Form: KIT | Route: INTRAVENOUS
Manufacturer: Amgen, Inc
Category: prescription | Type: HUMAN PRESCRIPTION DRUG LABEL
Date: 20251119

ACTIVE INGREDIENTS: TARLATAMAB 0.9 mg/1 mg
INACTIVE INGREDIENTS: SUCROSE 37.1 mg/1 mg; GLUTAMIC ACID 0.72 mg/1 mg; POLYSORBATE 80 0.04 mg/1 mg; SODIUM HYDROXIDE; CITRIC ACID MONOHYDRATE 36.75 mg/1 mL; LYSINE HYDROCHLORIDE 1598.8 mg/1 mL; POLYSORBATE 80 7 mg/1 mL; SODIUM HYDROXIDE

HIGHLIGHTS OF PRESCRIBING INFORMATION

These highlights do not include all the information needed to use IMDELLTRA® safely and effectively. See full prescribing information for IMDELLTRA.
IMDELLTRA® (tarlatamab-dlle) for injection, for intravenous use
Initial U.S. Approval: 2024

WARNING: CYTOKINE RELEASE SYNDROME and NEUROLOGIC TOXICITY including IMMUNE EFFECTOR CELL-ASSOCIATED NEUROTOXICITY SYNDROME

See full prescribing information for complete boxed warning.

Cytokine release syndrome (CRS), including life-threatening or fatal reactions, can occur in patients receiving IMDELLTRA. Initiate treatment with the IMDELLTRA using step-up dosing schedule to reduce the incidence and severity of CRS. Withhold IMDELLTRA until CRS resolves or permanently discontinue based on severity. (2.5, 5.1)

Neurologic toxicity and Immune Effector Cell-Associated Neurotoxicity Syndrome (ICANS), including life-threatening or fatal reactions, can occur in patients receiving IMDELLTRA. Monitor patients for signs or symptoms of neurologic toxicity, including ICANS, during treatment and treat promptly. Withhold IMDELLTRA until ICANS resolves or permanently discontinue based on severity. (2.5, 5.2)

RECENT MAJOR CHANGES

Indications and Usage (1) | 11/2025
Dosage and Administration (2.1, 2.2, 2.3) | 11/2025
Dosage and Administration (2.4, 2.5, 2.6) | 11/2025
Warnings and Precautions (5.1, 5.2, 5.3, 5.4) | 11/2025
Warnings and Precautions, (5.5,5.6,5.7) | 11/2025

1 INDICATIONS AND USAGE

IMDELLTRA is a bispecific delta-like ligand 3 (DLL3)-directed CD3 T- cell engager indicated for the treatment of adult patients with extensive stage small cell lung cancer (ES-SCLC) with disease progression on or after platinum-based chemotherapy. (1)

2 DOSAGE AND ADMINISTRATION

Administer as an intravenous infusion over 1 hour. (2.2)

- Administer IMDELLTRA according to the step-up dosing schedule in Table 1 to reduce the risk of cytokine release syndrome. (2.2)
- Administer concomitant medications as recommended. (2.3)
- Monitor patients from the start of the IMDELLTRA infusion for 22 to 24 hours on Cycle 1 Day 1 and Cycle 1 Day 8 in an appropriate healthcare setting.
- Recommend patients to remain within 1 hour of an appropriate healthcare setting for a total of 48 hours from the start of the infusion with IMDELLTRA following Cycle 1 Day 1 and Cycle 1 Day 8 doses, accompanied by a caregiver. (2.2)
- See Full Prescribing Information for instructions on preparation and administration. (2.2, 2.6)

3 DOSAGE FORMS AND STRENGTHS

- For injection: 1 mg of lyophilized powder in a single-dose vial for reconstitution and further dilution. (3)
- For injection: 10 mg of lyophilized powder in a single-dose vial for reconstitution and further dilution. (3)

4 CONTRAINDICATIONS

None. (4)

5 WARNINGS AND PRECAUTIONS

- Cytopenias: Monitor complete blood counts prior to administration of all doses of IMDELLTRA up through Cycle 5 Day 15 and then prior to administration of IMDELLTRA on Day 1 of each cycle starting with Cycle 6. More frequent evaluation may be necessary as clinically indicated. Withhold or permanently discontinue based on severity. (5.3)
- Infections: Monitor for signs and symptoms of infection; treat appropriately. Withhold or permanently discontinue based on severity. (5.4)
- Hepatotoxicity: Monitor liver enzymes and bilirubin prior to administration of all doses of IMDELLTRA up through Cycle 5 Day 15 and then prior to administration of IMDELLTRA on Day 1 of each cycle starting with Cycle 6. More frequent evaluation may be necessary as clinically indicated. Withhold or permanently discontinue based on severity. (5.5)
- Hypersensitivity: Monitor for signs and symptoms of hypersensitivity and treat accordingly. Withhold or permanently discontinue based on severity. (5.6)
  Embryo-Fetal Toxicity: May cause fetal harm. Advise females of reproductive potential of the potential risk to the fetus and to use effective contraception (5.7, 8.1, 8.3)

6 ADVERSE REACTIONS

- The most common adverse reactions (> 20%) were cytokine release syndrome, fatigue, decreased appetite, anemia, dysgeusia, pyrexia, constipation, musculoskeletal pain, and nausea.
- The most common (≥ 5%) Grade 3 or 4 laboratory abnormalities were decreased lymphocytes, decreased sodium, decreased total neutrophils, and increased uric acid.

To report SUSPECTED ADVERSE REACTIONS, contact Amgen Inc. at 1-800-77-AMGEN (1-800-772-6436) or FDA at 1-800-FDA-1088 or www.fda.gov/medwatch.

8 USE IN SPECIFIC POPULATIONS

Lactation: Advise not to breastfeed. (8.2)

FULL PRESCRIBING INFORMATION

WARNING: CYTOKINE RELEASE SYNDROME and NEUROLOGIC TOXICITY including IMMUNE EFFECTOR CELL-ASSOCIATED NEUROTOXICITY SYNDROME

Cytokine release syndrome (CRS), including life-threatening or fatal reactions, can occur in patients receiving IMDELLTRA. Initiate IMDELLTRA using the step-up dosing schedule to reduce the incidence and severity of CRS. Withhold IMDELLTRA until CRS resolves or permanently discontinue based on severity [see Dosage and Administration (2.5) and Warnings and Precautions (5.1)].

Neurologic toxicity and immune effector cell-associated neurotoxicity syndrome (ICANS), including life-threatening or fatal reactions, can occur in patients receiving IMDELLTRA. Monitor patients for signs and symptoms of neurologic toxicity, including ICANS, during treatment and treat promptly. Withhold IMDELLTRA until ICANS resolves or permanently discontinue based on severity [see Dosage and Administration (2.5) and Warnings and Precautions (5.2)].

1 INDICATIONS AND USAGE

IMDELLTRA is indicated for the treatment of adult patients with extensive stage small cell lung cancer (ES-SCLC) with disease progression on or after platinum-based chemotherapy.

2 DOSAGE AND ADMINISTRATION

2.1 Important Dosage and Administration Information

- Administer IMDELLTRA according to the step-up dose and schedule in Table 1 to reduce the incidence and severity of cytokine release syndrome (CRS) [see Dosage and Administration (2.2)].
- Evaluate complete blood count, liver enzymes and bilirubin prior to administration of all doses of IMDELLTRA up through Cycle 5 Day 15 and then prior to administration of IMDELLTRA on Day 1 of each cycle starting with Cycle 6. More frequent evaluation may be necessary if clinically indicated [see Warnings and Precautions (5.3, 5.5)].
- Ensure patients are well hydrated prior to administration of IMDELLTRA [see Warnings and Precautions (5.1)].
- For Cycle 1, administer recommended concomitant medications in Table 3 before and after Cycle 1 Day 1 and Cycle 1 Day 8 IMDELLTRA infusions to reduce the risk of CRS reactions [see Dosage and Administration (2.3)].
- IMDELLTRA should only be administered by a qualified healthcare professional with appropriate medical support to manage severe reactions, such as CRS and neurologic toxicity, including immune effector cell-associated neurotoxicity syndrome (ICANS) [see Warnings and Precautions (5.1, 5.2)].
- Due to the risk of CRS and neurologic toxicity, including ICANS, monitor patients from the start of the IMDELLTRA infusion for 22 to 24 hours on Cycle 1 Day 1 and Cycle 1 Day 8 in an appropriate healthcare setting [see Dosage and Administration (2.5) and Warnings and Precautions (5.1, 5.2)].
- Recommend patients to remain within 1 hour of an appropriate healthcare setting for a total of 48 hours from start of the infusion with IMDELLTRA following Cycle 1 Day 1 and Cycle 1 Day 8 doses, accompanied by a caregiver.
- Inform both the patient and the caregiver on the signs and symptoms of cytokine release syndrome (CRS) and immune effector cell-associated neurotoxicity syndrome (ICANS) prior to discharge.

2.2 Recommended Dosage and Administration

- Administer IMDELLTRA as an intravenous infusion for one hour.
- The recommended step-up dose and schedule for IMDELLTRA is provided in Table 1. Administer step-up dose and schedule on Cycle 1 Day 1 to reduce the incidence and severity of CRS.
- After step-up dose and schedule on Cycle 1 Day 1, administer IMDELLTRA every 2 weeks until disease progression or unacceptable toxicity.

Table 1. Recommended Dose and Schedule of IMDELLTRA
Dosing Schedule | Day | Dose of IMDELLTRA | Administration Instructions | Recommended Monitoring
Step-up Dose and Schedule Cycle 1 | Day 1 [Administer recommended concomitant medications before and after Cycle 1 Day 1 and Cycle 1 Day 8 IMDELLTRA infusions as described in Table 3.] | Step-up dose 1 mg | Administer IMDELLTRA as a 1-hour intravenous infusion in an appropriate healthcare setting. | Monitor patients from the start of the IMDELLTRA infusion for 22 to 24 hours on Cycle 1 Day 1 and Cycle 1 Day 8 in an appropriate healthcare setting. Recommend that patients remain within 1 hour of an appropriate healthcare setting for a total of 48 hours from start of the IMDELLTRA infusion accompanied by a caregiver.
Step-up Dose and Schedule Cycle 1 | Day 8 | 10 mg | Administer IMDELLTRA as a 1-hour intravenous infusion in an appropriate healthcare setting. | Monitor patients from the start of the IMDELLTRA infusion for 22 to 24 hours on Cycle 1 Day 1 and Cycle 1 Day 8 in an appropriate healthcare setting. Recommend that patients remain within 1 hour of an appropriate healthcare setting for a total of 48 hours from start of the IMDELLTRA infusion accompanied by a caregiver.
Step-up Dose and Schedule Cycle 1 | Day 15 | 10 mg | Administer IMDELLTRA as a 1-hour intravenous infusion in an appropriate healthcare setting. | Observe patients for 6-8 hours post IMDELLTRA infusion [Extended monitoring in a healthcare setting is not required unless the patient experiences Grade ≥ 2 CRS, ICANS or neurological toxicity during prior treatments. See Tables 5 and 6 for monitoring recommendations.]
Cycle 2 | Day 1 and 15 | 10 mg | Administer IMDELLTRA as a 1-hour intravenous infusion in an appropriate healthcare setting. | Observe patients for 6-8 hours post IMDELLTRA infusion.
Cycles 3 and 4 | Day 1 and 15 | 10 mg | Administer IMDELLTRA as a 1-hour intravenous infusion in an appropriate healthcare setting. | Observe patients for 3-4 hours post IMDELLTRA infusion.
Cycle 5 and subsequent infusions | Day 1 and 15 | 10 mg | Administer IMDELLTRA as a 1-hour intravenous infusion in an appropriate healthcare setting. | Observe patients for 2 hours post IMDELLTRA infusion.
Note: See Table 4 for recommendation on restarting IMDELLTRA after dose delays.

Administration

- The intravenous (IV) catheter for concomitant medications administration can be used to administer the IMDELLTRA infusion.
- To ensure patency, flush the IV catheter over 3 to 5 minutes using 0.9% Sodium Chloride for Injection.
- Administer the reconstituted and diluted IMDELLTRA as a 1-hour intravenous infusion at a constant flow rate using an infusion pump. The pump should be programmable, lockable, non-elastomeric, and have an alarm. Flush the IV-line upon completion of the IMDELLTRA infusion.

Table 2 provides the infusion duration and rate.

Table 2. IMDELLTRA Infusion Duration and Rate
Infusion Duration for 250 mL IV Preparation | Infusion Rate
1 hour | 250 mL/hour

2.3 Recommended Concomitant Medications for IMDELLTRA Administration for Cycle 1 Day 1 and Cycle 1 Day 8

Administer recommended concomitant medications for IMDELLTRA during Cycle 1 Day 1 and Cycle 1 Day 8 as presented in Table 3 to reduce the risk of CRS [see Warnings and Precautions (5.1)].

Table 3. Recommended Concomitant Medications for IMDELLTRA Administration for Cycle 1 Day 1 and Cycle 1 Day 8
Treatment Day | Medication | Administration
Cycle 1 Day 1 and Cycle 1 Day 8 | Administer dexamethasone 8 mg intravenously (or equivalent) | Within 1 hour prior to IMDELLTRA administration
Cycle 1 Day 1 and Cycle 1 Day 8 | Administer 1 liter of normal saline intravenously over 2 to 4 hours | Immediately after completion of IMDELLTRA infusion

2.4 Restarting IMDELLTRA After Dosage Delay

If a dose of IMDELLTRA is delayed, restart based on the recommendation as listed in Table 4 and resume the dose and schedule accordingly [see Dosage and Administration (2.2)].

Administer recommended concomitant medications as indicated in Table 3.

Table 4. Recommendations for Restarting IMDELLTRA After Dosage Delay
Last Dose Administered | Time Since the Last Dose Administered | Action [Administer recommended concomitant medications before and after Cycle 1 Day 1 and Cycle 1 Day 8 IMDELLTRA infusions and monitor patients accordingly [see Dosage and Administration (2.1, 2.2 and 2.3)].]
1 mg on Cycle 1 Day 1 | 2 weeks or less (≤ 14 days) | Administer IMDELLTRA 10 mg, then resume with the planned dose and schedule.
1 mg on Cycle 1 Day 1 | Greater than 2 weeks (> 14 days) | Administer IMDELLTRA step-up dose 1 mg. If tolerated, increase to 10 mg 1 week later. Then resume with the planned dose and schedule.
10 mg on Cycle 1 Day 8 | 3 weeks or less (≤ 21 days) | Administer IMDELLTRA 10 mg, then resume with the planned dose and schedule.
10 mg on Cycle 1 Day 8 | Greater than 3 weeks (> 21 days) | Administer IMDELLTRA step-up dose 1 mg. If tolerated, increase to 10 mg 1 week later. Then resume with the planned dose and schedule.
10 mg on Cycle 1 Day 15 and subsequent Cycles every 2 weeks thereafter | 4 weeks or less (≤ 28 days) | Administer IMDELLTRA 10 mg, then resume with the planned dose and schedule.
10 mg on Cycle 1 Day 15 and subsequent Cycles every 2 weeks thereafter | Greater than 4 weeks (> 28 days) | Administer IMDELLTRA step-up dose 1 mg. If tolerated, increase to 10 mg 1 week later. Then resume with the planned dose and schedule.

2.5 IMDELLTRA Dosage Modifications and Adverse Reaction Management

No dose reduction for IMDELLTRA is recommended. See Table 5 and Table 6 for recommended management of CRS, neurologic toxicity including ICANS respectively and Table 7 for cytopenias, infections and other adverse reactions.

Cytokine Release Syndrome (CRS)

Diagnose CRS based on clinical presentation [see Warnings and Precautions (5.1)]. Evaluate for and treat other causes of fever, hypoxia, and hypotension.

If CRS is suspected, manage according to the recommendations in Table 5. Monitor patients who experience Grade 2 or higher CRS (e.g., hypotension not responsive to fluids, or hypoxia requiring supplemental oxygen) with continuous cardiac telemetry and pulse oximetry.

For severe or life-threatening CRS, recommend administering tocilizumab or equivalent therapy and intensive monitoring (e.g., ICU) for supportive therapy. Perform laboratory testing to monitor for disseminated intravascular coagulation (DIC), hematology parameters, as well as pulmonary, cardiac, renal, and hepatic function. Table 5 provides the guidelines for grading and dosage modification and management of cytokine release syndrome.

Table 5. Guidelines for Grading and Dosage Modification and Management of Cytokine Release Syndrome [CRS based on American Society for Transplantation and Cellular Therapy (ASTCT) Consensus Grading (2019).]
CRS Grade | Defining Symptoms | IMDELLTRA Dosage Modification | Management
Grade 1 | Symptoms require symptomatic treatment only (e.g., fever ≥ 100.4°F without hypotension or hypoxia). | Withhold IMDELLTRA until event resolves, then resume IMDELLTRA at the next scheduled dose [See Table 4 for recommendations on restarting IMDELLTRA after dose delays [see Dosage and Administration (2.4)].] . | - Administer symptomatic treatment (e.g., acetaminophen) for fever. - Consider dexamethasone 4 mg to 10 mg oral or IV (or equivalent) [Taper steroids per standard of care guidelines.] .
Grade 2 | Symptoms require and respond to moderate intervention. Fever ≥ 100.4°F,; - Hypotension responsive to fluids not requiring vasopressors and/or - Hypoxia requiring low flow nasal cannula or blow-by. | Withhold IMDELLTRA until event resolves, then resume IMDELLTRA at the next scheduled dose. | - Recommend hospitalization for a minimum of 24 hours with cardiac telemetry and pulse oximetry. - Administer symptomatic treatment (e.g., acetaminophen) for fever. - Administer supplemental oxygen and intravenous fluids when indicated. - Consider dexamethasone (or equivalent) 8 mg oral or IV. - Consider tocilizumab (or equivalent).; When resuming the next planned dose, monitor patients from the start of the IMDELLTRA infusion for 22 to 24 hours in an appropriate healthcare setting.
Grade 3 | Severe symptoms defined as temperature ≥ 100.4°F with:; - Hemodynamic instability requiring a vasopressor (with or without vasopressin) and/or - Worsening hypoxia or respiratory distress requiring high flow nasal cannula (> 6 L/min oxygen) or face mask. | Withhold IMDELLTRA until the event resolves, then resume IMDELLTRA at the next scheduled dose. For recurrent Grade 3 events, permanently discontinue IMDELLTRA. | In addition to Grade 2 treatment:; - Recommend intensive monitoring, e.g., ICU care. - Administer dexamethasonec (or equivalent) 8 mg IV every 8 hours up to 3 doses. - Vasopressor support as needed. - High flow oxygen support as needed. - Recommend tocilizumab (or equivalent).; Prior to the next dose, administer concomitant medications as recommended for Cycle 1 Day 1 and Cycle 1 Day 8 (see Table 3). When resuming the next planned dose, monitor patients from the start of the IMDELLTRA infusion for 22 to 24 hours in an appropriate healthcare setting.
Grade 4 | Life-threatening symptoms defined as temperature ≥ 100.4°F with:; - Hemodynamic instability requiring multiple vasopressors (excluding vasopressin). and/or Worsening hypoxia or respiratory distress despite oxygen administration requiring positive pressure. | Permanently discontinue IMDELLTRA. | - ICU care. - Per Grade 3 treatment. Recommend tocilizumab (or equivalent)

Neurologic Toxicity including ICANS

At the first sign of neurologic toxicity, including ICANS, withhold IMDELLTRA and consider neurology evaluation. Rule out other causes of neurologic symptoms. Provide supportive therapy, which may include intensive care, for severe or life-threatening neurologic toxicities, including ICANS [see Warnings and Precautions (5.2)]. Manage ICANS and neurologic toxicity according to the recommendations in Table 6 and consider further management per current practice guidelines.

Table 6. Guidelines for Management of Neurologic Toxicity including Immune Effector Cell-Associated Neurotoxicity Syndrome (ICANS) [ICANS based on American Society for Transplantation and Cellular Therapy (ASTCT) Consensus Grading (2019)]
ICANS Grade | Defining Symptoms | IMDELLTRA Dosage Modifications | Management
Grade 1 | ICE score 7-9 [If patient is arousable and able to perform Immune Effector Cell-Associated Encephalopathy (ICE) Assessment, assess: Orientation (oriented to year, month, city, hospital = 4 points); Naming (names 3 objects, e.g., point to clock, pen, button = 3 points); Following commands (e.g., "show me 2 fingers" or "close your eyes and stick out your tongue" = 1 point); Writing (ability to write a standard sentence = 1 point); and Attention (count backwards from 100 by ten = 1 point). If patient is unarousable and unable to perform ICE Assessment (Grade 4 ICANS) = 0 points] with no depressed level of consciousness. | - Withhold IMDELLTRA until ICANS resolves, then resume IMDELLTRA at the next scheduled dose [See Table 4 for recommendations on restarting IMDELLTRA after dose delays [see Dosage and Administration (2.4)]] . | - Supportive care.
Grade 2 | ICE score 3-6 and/or mild somnolence awaking to voice. | - Withhold IMDELLTRA until ICANS resolves, then resume IMDELLTRA at the next scheduled dose. | - Supportive care. - Dexamethasone [Taper steroids per standard of care guidelines] (or equivalent) 8 to 10 mg oral or IV. Can repeat every 12 hours or methylprednisolone (or equivalent) 1 mg/kg IV every 12 hours if symptoms worsen. - Monitor neurologic symptoms and consider consultation with neurologist and other specialists for further evaluation and management. - Monitor patients from the start of the IMDELLTRA infusion for 22 to 24 hours following the next dose of IMDELLTRA.
Grade 3 | ICE score 0-2 and/or depressed level of consciousness awakening only to tactile stimulus and/or any clinical seizure focal or generalized that resolves rapidly or nonconvulsive seizures on EEG that resolve with intervention and/or Focal or local edema on neuroimaging. | - Withhold IMDELLTRA until the ICANS resolves, then resume IMDELLTRA at the next scheduled dose. - If there is no improvement to Grade ≤ 1 within 7 days permanently discontinue IMDELLTRA. - For recurrent Grade 3 events, permanently discontinue IMDELLTRA. | - Recommend intensive monitoring, e.g., ICU care. - Consider mechanical ventilation for airway protection. Dexamethasone (or equivalent) 10 mg IV every 6 hours or methylprednisolone (or equivalent) 1 mg/kg IV every 12 hours. - Consider repeat neuroimaging (CT or MRI) every 2-3 days if patient has persistent Grade ≥ 3 neurotoxicity. Monitor patients from the start of the IMDELLTRA infusion for 22 to 24 hours following the next dose of IMDELLTRA.
Grade 4 | ICE score 0 (patient is unarousable and unable to perform ICE) and/or Stupor or coma and/or Life-threatening prolonged seizure (> 5 minutes) or repetitive clinical or electrical seizures without return to baseline in between and/or diffuse cerebral edema on neuroimaging, decerebrate or decorticate posturing or papilledema, cranial nerve VI palsy, or Cushing's triad. | - Permanently discontinue IMDELLTRA. | - ICU care. - Consider mechanical ventilation for airway protection. - High dose corticosteroids (e.g., methylprednisolone 1000 mg/day in divided doses IV for 3 days). - Consider repeat neuroimaging (CT or MRI) every 2-3 days if patient has persistent Grade ≥ 3 neurotoxicity. - Treat convulsive status epilepticus per institutional guidelines.

Table 7. Recommended Treatment Interruptions of IMDELLTRA for the Management of Cytopenias, Infections, and Other Adverse Reactions
Adverse Reactions | Severity [Severity based on National Cancer Institute Common Terminology Criteria for Adverse Events (NCI CTCAE) Version 5.0.] | Dosage Modification [Refer to Table 4 for dose restarting guidance.]
Cytopenias [see Warnings and Precautions (5.3)] | Grade 3 Neutropenia | Withhold IMDELLTRA until recovery to Grade ≤ 2. Consider administration of granulocyte colony stimulating factor (G-CSF). Permanently discontinue if recovery to Grade ≤ 2 does not occur within 3 weeks.
Cytopenias [see Warnings and Precautions (5.3)] | Grade 4 Neutropenia | Withhold IMDELLTRA until recovery to Grade ≤ 2. Consider administration of granulocyte colony stimulating factor (G-CSF). Permanently discontinue if recovery to Grade ≤ 2 does not occur within 1 week.
Cytopenias [see Warnings and Precautions (5.3)] | Recurrent Grade 4 Neutropenia | Permanently discontinue IMDELLTRA
Cytopenias [see Warnings and Precautions (5.3)] | Febrile neutropenia | Withhold IMDELLTRA until neutropenia recovers to Grade ≤ 2 and fever resolves.
Cytopenias [see Warnings and Precautions (5.3)] | Hemoglobin <8 g/dL | Withhold IMDELLTRA until hemoglobin is ≥8 g/dL.
Cytopenias [see Warnings and Precautions (5.3)] | Grade 3 or Grade 4 Decreased platelet count | Withhold IMDELLTRA until platelet count is Grade ≤ 2 and no evidence of bleeding. Permanently discontinue if recovery to Grade ≤ 2 does not occur within 3 weeks.
Cytopenias [see Warnings and Precautions (5.3)] | Recurrent Grade 4 Decreased platelet count | Permanently discontinue IMDELLTRA.
Infections [see Warnings and Precautions (5.4)] | All Grades | Withhold IMDELLTRA in the step-up phase in patients until infection resolves.
Infections [see Warnings and Precautions (5.4)] | Grade 3 | Withhold IMDELLTRA during the treatment phase until infection improves to Grade ≤ 1.
Infections [see Warnings and Precautions (5.4)] | Grade 4 | Permanently discontinue IMDELLTRA.
Hepatotoxicity [see Warnings and Precautions (5.5)] | Grade 3 Increased ALT or AST or bilirubin | Withhold IMDELLTRA until improved to Grade ≤ 1.
Hepatotoxicity [see Warnings and Precautions (5.5)] | Grade 4 Increased ALT or AST or bilirubin | Permanently discontinue IMDELLTRA.
Hepatotoxicity [see Warnings and Precautions (5.5)] | AST or ALT > 3 × ULN with total bilirubin > 2 × ULN in the absence of alternative causes | Permanently discontinue IMDELLTRA.
Other Adverse Reactions [see Adverse Reactions (6.1)] | Grade 3 or 4 | Withhold IMDELLTRA until recovery to Grade ≤ 1 or baseline. Consider permanently discontinuing if adverse reaction does not resolve within 28 days. Consider permanent discontinuation for Grade 4 events.

2.6 Preparation

Material Compatibility Information

- IV bags composed of ethyl vinyl acetate (EVA), polyolefin, and polyvinyl chloride (PVC) have been shown to be compatible with IMDELLTRA at the specified administration conditions.
- IV line and catheter materials composed of polyolefin, PVC, and polyurethane have been shown to be compatible with IMDELLTRA at the specified administration conditions.
- The use of Closed System Transfer Device (CSTD) is not recommended due to potential wrong dose medication error risk. Amgen has not performed compatibility testing of vial adaptor CSTDs with IMDELLTRA.

Step 1: Reconstitute IMDELLTRA with Sterile Water for Injection

- Table 8 provides the required amount of sterile water for injection required to reconstitute IMDELLTRA 1 mg and 10 mg vials.

Do not use IV Solution Stabilizer (IVSS) to reconstitute IMDELLTRA.

The IV Solution Stabilizer (IVSS) is used to coat the intravenous bag prior to addition of reconstituted IMDELLTRA to prevent adsorption of IMDELLTRA to IV bags and IV tubing.

Table 8. Required Amount of Sterile Water for Injection to Reconstitute IMDELLTRA [Each vial contains overfill to allow for withdrawal of 1.1 mL (1 mg vial) or 4.2 mL (10 mg vial) after reconstitution to ensure delivery at the stated concentration of labeled vial strength.]
IMDELLTRA Vial Strength | Amount of Sterile Water for Injection Needed to Reconstitute IMDELLTRA | Resulting Concentration
1 mg | 1.3 mL | 0.9 mg/mL
10 mg | 4.4 mL | 2.4 mg/mL

- Using a needle and syringe filled with the required amount of sterile water, inject the sterile water against the glass vial. Avoid injecting the water directly onto the powder to prevent foaming.
- Gently swirl the contents to mix. Do not shake.
- Inspect parenteral drug products for particulate matter and discoloration prior to administration. Inspect that the solution is clear to opalescent, colorless to slightly yellow. Do not use if the solution is cloudy or has particulates.
- Further dilute reconstituted IMDELLTRA.
- The reconstituted IMDELLTRA must be further diluted within 4 hours of reconstitution or discarded.

Prepare the infusion bag: Steps 2 to 5

Step 2 : Withdraw 0.9% Sodium Chloride for Injection

- Using a 250 mL prefilled bag of 0.9% Sodium Chloride for Injection, withdraw the amount of sodium chloride specified in Table 9 and discard.

Table 9. Required Amount of 0.9% Sodium Chloride to Withdraw from 250 mL IV Bag
IMDELLTRA Vial Strength | IMDELLTRA Dose | Volume of 0.9% Sodium Chloride to Withdraw From 250 mL IV Bag
1 mg | 1 mg | 14 mL
10 mg | 10 mg | 17 mL

Step 3: Add IV Solution Stabilizer to the infusion bag

- Inject 13 mL of IV Solution Stabilizer (IVSS) into the 250 mL 0.9% Sodium Chloride infusion bag, see Table 10.
- Gently mix the contents of the infusion bag to avoid foaming. Do not shake.

Table 10. Required Amount of IV Solution Stabilizer (IVSS) to Add to IV Bag
IMDELLTRA Vial Strength | IMDELLTRA Dose | Volume of IV Solution Stabilizer (IVSS) to Add to IV Bag
1 mg | 1 mg | 13 mL
10 mg | 10 mg | 13 mL

Step 4: Dilute the reconstituted IMDELLTRA into the infusion bag

- Transfer the required volume of reconstituted IMDELLTRA listed in Table 11 to the infusion bag (containing IV Solution Stabilizer).

NOTE: The final concentrations for the different strength vials are NOT the same following reconstitution and further dilution.

Table 11. Required Amount of Reconstituted IMDELLTRA to Add to 250 mL IV Bag
IMDELLTRA Vial Strength | IMDELLTRA Dose | Volume of Reconstituted IMDELLTRA to Add to 250 mL IV Bag
1 mg | 1 mg | 1.1 mL
10 mg | 10 mg | 4.2 mL

- Gently mix the contents of the bag. Do not shake.

Step 5: Remove air from IV bag

Remove air from the prepared IV bag using an empty syringe to avoid foaming.

Step 6: Prime IV tubing

- Prime intravenous tubing with either 0.9% Sodium Chloride for Injection or with the final prepared product.
- See Table 12 for maximum storage time of prepared IMDELLTRA infusion.

Prepared IMDELLTRA Infusion Bag Storage Requirements

- Administer reconstituted and diluted IMDELLTRA immediately.
- Table 12 displays the maximum storage time for the prepared IMDELLTRA infusion bag.
- Maximum storage time includes total duration from the time of reconstitution of the vial of IMDELLTRA to the end of the infusion.

Table 12. Maximum Storage Time for Prepared IMDELLTRA Infusion Bag
 | Room Temperature 20°C to 25°C (68°F to 77°F) | Refrigerated 2°C to 8°C (36°F to 46°F)
Prepared IMDELLTRA Infusion Bag | 8 hours | 7 days
- Discard the prepared IMDELLTRA infusion bag after maximum storage time (from time of reconstitution).
- If refrigerated, allow the prepared IMDELLTRA infusion bag to come room temperature prior to administration, and complete the infusion within 8 hours (including preparation and infusion time).
- Do not re-refrigerate prepared infusion bag.

3 DOSAGE FORMS AND STRENGTHS

For injection: 1 mg of white to slightly yellow lyophilized powder in a single-dose vial for reconstitution and further dilution.

For injection: 10 mg of white to slightly yellow lyophilized powder in a single-dose vial for reconstitution and further dilution.

4 CONTRAINDICATIONS

None.

5 WARNINGS AND PRECAUTIONS

5.1 Cytokine Release Syndrome

IMDELLTRA can cause cytokine release syndrome (CRS) including life-threatening or fatal reactions.

In the pooled safety population [see Adverse Reactions (6.1)], CRS occurred in 57% (268/473) of patients who received IMDELLTRA, including 39% Grade 1, 15% Grade 2, 1.7% Grade 3 and 0.2% Grade 4. Recurrent CRS occurred in 24% of IMDELLTRA-treated patients including 20% Grade 1 and 3.4% Grade 2; one patient experienced recurrent Grade 3.

Among the 268 patients who experienced CRS, 73% had CRS after the first dose, 60% had CRS after the second dose, and 15% had CRS following the third or later dose. Following the Cycle 1 Day 1, Day 8, Day 15 infusions, 24%, 8%, and 1% of patients experienced Grade ≥ 2 CRS, respectively. From Cycle 2 onwards, 1.5% of patients experienced Grade ≥ 2 CRS. Of the patients who experienced CRS, 31% received steroids and 10% required tocilizumab. The median time to onset of all grade CRS from most recent dose of IMDELLTRA was 16 hours (range: start of infusion to 15 days). The median time to onset of Grade ≥ 2 CRS from most recent dose of IMDELLTRA was 15 hours (range: start of infusion to 15 days).

Clinical signs and symptoms of CRS included pyrexia, hypotension, fatigue, tachycardia, headache, hypoxia, nausea and vomiting. Potentially life-threatening complications of CRS may include cardiac dysfunction, acute respiratory distress syndrome, neurologic toxicity, renal and/or hepatic failure, and disseminated intravascular coagulation (DIC).

Administer IMDELLTRA following the recommended step-up dosing and administer concomitant medications before and after Cycle 1 Day 1 and Cycle 1 Day 8 IMDELLTRA infusions as described in Table 3 to reduce the risk of CRS [see Dosage and Administration (2.3)]. Administer IMDELLTRA in an appropriate healthcare facility equipped to monitor and manage CRS. Ensure patients are well hydrated prior to administration of IMDELLTRA.

Closely monitor patients for signs and symptoms of CRS during treatment with IMDELLTRA. At the first sign of CRS, immediately discontinue IMDELLTRA infusion, evaluate the patient for hospitalization and institute supportive care based on severity. Withhold or permanently discontinue IMDELLTRA based on severity [see Dosage and Administration (2.5)]. Counsel patients and caregivers to seek medical attention should signs or symptoms of CRS occur.

5.2 Neurologic Toxicity Including ICANS

IMDELLTRA can cause life-threatening or fatal neurologic toxicity including ICANS.

In the pooled safety population [see Adverse Reactions (6.1)], neurologic toxicity occurred in 65% of patients who received IMDELLTRA, with Grade 3 or higher events in 7% of patients including fatal events in 0.2%. The most frequent neurologic toxicities were dysgeusia (34%), headache (17%), peripheral neuropathy (9%), dizziness (9%), and insomnia (8%).

The incidence of signs and symptoms consistent with ICANS was 10% in IMDELLTRA- treated patients, including events with the preferred terms: ICANs (4.7%), muscular weakness (3.2%), cognitive disorder (0.6%), aphasia (0.6%), depressed level of consciousness (0.4%), seizures (0.4%), encephalopathy (0.4%), and leukoencephalopathy (0.2%). There was one fatal reaction of ICANS [see Adverse Reactions (6.1)]. Recurrent ICANS occurred in 1.5% of patients. Of the patients who experienced ICANS, most experienced the event following Cycle 1 Day 1 (2.5%) and Cycle 1 Day 8 (3.6%). Following Day 1, Day 8, and Day 15 infusions, 1.3%, 1.3% and 0.4% of patients experienced Grade ≥ 2 ICANS, respectively. ICANS can occur several weeks following administration of IMDELLTRA. The median time to onset of ICANS from the first dose of IMDELLTRA was 16 days (range: 1 to 862 days). The median time to resolution of ICANS was 4 days (range: 1 to 40 days).

The onset of ICANS can be concurrent with CRS, following resolution of CRS, or in the absence of CRS. Clinical signs and symptoms of ICANS may include but are not limited to confusional state, depressed level of consciousness, disorientation, somnolence, lethargy, and bradyphrenia.

Patients receiving IMDELLTRA are at risk of neurologic adverse reactions and ICANS resulting in depressed level of consciousness. Advise patients to refrain from driving and engaging in hazardous occupations or activities, such as operating heavy or potentially dangerous machinery, until neurologic symptoms resolve.

Closely monitor patients for signs and symptoms of neurologic toxicity and ICANS during treatment with IMDELLTRA. At the first sign of ICANS, immediately discontinue the infusion, evaluate the patient and provide supportive therapy based on severity.

Withhold IMDELLTRA or permanently discontinue based on severity [see Dosage and Administration (2.5)].

5.3 Cytopenias

IMDELLTRA can cause cytopenias including neutropenia, thrombocytopenia, and anemia.

In the pooled safety population, [see Adverse Reactions (6.1)] based on laboratory data, decreased neutrophils occurred in 16% of patients, including 9% Grade 3 or 4. The median time to onset for Grade 3 or 4 decreased neutrophil count was 41 days (range: 2 to 306 days). Decreased platelets occurred in 30%, including 2.2% Grade 3 or 4. The median time to onset for Grade 3 or 4 decreased platelets was 67 days (range: 3 to 420 days). Decreased hemoglobin occurred in 56% of patients, including 4.7% Grade 3 or 4.

Febrile neutropenia was reported as an adverse event in 1.5% of patients treated with IMDELLTRA.

Monitor patients for signs and symptoms of cytopenias. Perform complete blood counts prior to treatment with all doses of IMDELLTRA, up through Cycle 5 Day 15 and then prior to administration of IMDELLTRA on Day 1 of each cycle starting with Cycle 6.

Based on the severity of cytopenias, temporarily withhold or permanently discontinue IMDELLTRA [see Dosage and Administration (2.5)].

5.4 Infections

IMDELLTRA can cause serious infections, including life-threatening and fatal infections.

In the pooled safety population, [see Adverse Reactions (6.1)], infections including opportunistic infections occurred in 43% of patients who received IMDELLTRA, including 14% Grade 3 or 4. The most frequent infections were pneumonia (11%), urinary tract infection (9%), COVID-19 (6%), upper respiratory tract infection (4.7%), respiratory tract infection (4%), candida infection (2.1%), oral candidiasis (2.1%) and nasopharyngitis (2.1%).

Monitor patients for signs and symptoms of infection prior to and during treatment with IMDELLTRA and treat as clinically indicated. Withhold or permanently discontinue IMDELLTRA based on severity [see Dosage and Administration (2.5)].

5.5 Hepatotoxicity

IMDELLTRA can cause hepatotoxicity.

In the pooled safety population [see Adverse Reactions (6.1)], based on laboratory data, elevated ALT occurred in 39% of patients who received IMDELLTRA, including 2.5% Grade 3 or 4 ALT. Elevated AST occurred in 43% of patients, including 3.2% Grade 3 or 4. Elevated bilirubin occurred in 16% of patients, including 1.3% Grade 3 or 4 [see Adverse Reactions (6.1)]. Liver enzyme elevation can occur with or without concurrent CRS.

Monitor liver enzymes and bilirubin prior to treatment with IMDELLTRA, and as clinically indicated. Withhold IMDELLTRA or permanently discontinue based on severity [see Dosage and Administration (2.5)].

5.6 Hypersensitivity

IMDELLTRA can cause severe hypersensitivity reactions.

Clinical signs and symptoms of hypersensitivity may include, but are not limited to, rash and bronchospasm.

Monitor patients for signs and symptoms of hypersensitivity during treatment with IMDELLTRA and manage as clinically indicated. Withhold or consider permanent discontinuation of IMDELLTRA based on severity [see Dosage and Administration (2.5)].

5.7 Embryo-Fetal Toxicity

Based on its mechanism of action, IMDELLTRA may cause fetal harm when administered to a pregnant woman. Advise patients of the potential risk to a fetus. Advise females of reproductive potential to use effective contraception during treatment with IMDELLTRA and for 2 months after the last dose [see Use in Specific Populations (8.1, 8.3)].

6 ADVERSE REACTIONS

The following clinically significant adverse reactions are described elsewhere in the labeling:

- Cytokine Release Syndrome (CRS) [see Warnings and Precautions (5.1)]
- Neurologic Toxicity Including ICANS [see Warnings and Precautions (5.2)]
- Cytopenias [see Warnings and Precautions (5.3)]
- Infections [see Warnings and Precautions (5.4)]
- Hepatotoxicity [see Warnings and Precautions (5.5)]
- Hypersensitivity [see Warnings and Precautions (5.6)]

6.1 Clinical Trials Experience

Because clinical trials are conducted under widely varying conditions, adverse reaction rates observed in the clinical trials of a drug cannot be directly compared to rates in the clinical trials of another drug and may not reflect the rates observed in practice.

The pooled safety population described in the WARNINGS AND PRECAUTIONS reflects exposure to intravenous IMDELLTRA, as a single agent, at the recommended dosage of IMDELLTRA 1 mg on Cycle 1 Day 1 followed by 10 mg on Days 8 and 15, and then every 2 weeks until disease progression or intolerable toxicity in 473 patients with small cell lung cancer enrolled in three clinical trials: DeLLphi-300, DeLLphi-301 and DeLLphi-304. Among 473 patients who received IMDELLTRA, 40% were exposed for 6 months or longer and 19% were exposed for greater than one year. The most common (≥ 20%) adverse reactions were CRS (57%), fatigue (48%), decreased appetite (38%), dysgeusia (34%), pyrexia (33%), constipation (31%), musculoskeletal pain (31%), and nausea (25%). The most common (≥ 5%) Grade 3 or 4 laboratory abnormalities were decreased lymphocytes (43%), decreased sodium (12%), decreased total neutrophils (9%), and increased uric acid (6%).

Extensive Stage Small Cell Lung Cancer

The safety of IMDELLTRA was evaluated in 252 patients in DeLLphi-304, a multicenter, randomized, open label trial in patients with extensive stage small cell lung cancer (ES- SCLC) with disease progression following treatment with platinum-based chemotherapy with or without an anti-PD-(L)1 antibody [see Clinical Studies (14.1)]. Patients received IMDELLTRA (n=252) or investigator's choice or investigator's choice of topotecan [n=176], lurbinectedin [n=45] or amrubicin [n=23].

Among patients who received IMDELLTRA, 41% were exposed for 6 months or longer and 18% were exposed for greater than one year.

The demographic characteristics of patients who received IMDELLTRA were: median age 64 years (range: 20 to 86); 71% male; 60% White, 38 % Asian, 0.8% Black or African American; and 4.8% were of Hispanic or Latino ethnicity.

Serious adverse reactions occurred in 52% of patients who received IMDELLTRA. Serious adverse reactions in >3% of patients included CRS (17%), pyrexia (6%), pneumonia (5%) and ICANS (3.6%). Fatal adverse reactions occurred in 8% of patients who received IMDELLTRA, including one fatal adverse reaction of ICANS (0.4%). Fatal adverse reactions occurring in more than one patient included pneumonia (1.6%), cardio-respiratory arrest (1.6%), and sepsis (0.8%).

Permanent discontinuation of IMDELLTRA due to an adverse reaction occurred in 6% of patients. Adverse reactions which resulted in permanent discontinuation of IMDELLTRA in > 1% of patients included pneumonia (1.2%).

Dosage interruptions of IMDELLTRA due to an adverse reaction occurred in 38% of patients. Adverse reactions which required dosage interruption in ≥ 2% of patients included neutropenia (5%), fatigue (4.4%), pneumonia (4%), decreased appetite (2.8%), COVID-19 (2%).

Table 13 summarizes adverse reactions observed in DeLLphi-304.

Table 13. Adverse Reactions (≥ 15%) in Patients with SCLC Who Received IMDELLTRA in DeLLphi-304
Adverse Reaction | IMDELLTRA [Graded using CTCAE Version 4.0 and Version 5.0.] (N = 252) |  | Standard of Care (N = 244)
 | Any Grade (%) | Grade 3 or 4 (%) | Any Grade (%) | Grade 3 or 4 (%)
Immune system disorders
Cytokine release syndrome [Based on American Society for Transplantation and Cellular Therapy (ASTCT) 2019.] | 56 | 1.2 | 1.2 | 0
General disorders and administration site conditions
Fatigue [Includes fatigue and asthenia] | 39 | 6 | 43 | 10
Pyrexia [Includes body temperature increased, hyperthermia, pyrexia] | 29 | 1.2 | 11 | 1.2
Metabolism and nutrition disorders
Decreased appetite | 37 | 2 | 23 | 1.6
Gastrointestinal disorders
Constipation | 30 | 0.4 | 22 | 0
Nausea | 25 | 0.4 | 32 | 0
Nervous system disorders
Dysgeusia [Includes ageusia, dysgeusia, hypogeusia] | 28 | 0 | 2.5 | 0
Headache [Includes headache and tension headache] | 16 | 0 | 9 | 0
Musculoskeletal and connective tissue disorders
Musculoskeletal pain [Includes arthralgia, back pain, bone pain, musculoskeletal pain, myalgia, neck pain, non-cardiac chest pain, pain in extremity, spinal pain] | 27 | 1.6 | 21 | 2.5
Respiratory, thoracic and mediastinal disorders
Cough [Includes cough and productive cough] | 17 | 0 | 17 | 0

Clinically relevant adverse reactions occurring in < 15% of patients who received IMDELLTRA were immune effector cell-associated neurotoxicity syndrome, neurotoxicity, tremor, seizure, ataxia, confusional state, delirium, dyspnea, encephalopathy and weight decreased.

Table 14 summarizes laboratory abnormalities in DeLLphi-304.

Table 14. Laboratory Abnormalities (≥ 20%) That Worsened from Baseline in Patients with SCLC in DeLLphi-304
Laboratory Abnormality | IMDELLTRA [The denominator used to calculate the rate varied for IMDELLTRA (Range: 229 to 250) and SOC (Range: 205 to 226) based on the number of patients with a baseline value and at least one post-treatment value.] N=252 |  | Standard of care N=244
Laboratory Abnormality | All Grades (%) | Grade 3 or 4 (%) | All Grades (%) | Grade 3 or 4 (%)
Hematology
Lymphocytes decreased | 65 | 27 | 62 | 27
Hemoglobin decreased | 51 | 4.5 | 86 | 29
White blood cells decreased | 50 | 7 | 70 | 29
Platelets decreased | 25 | 0.4 | 55 | 20
Neutrophils decreased [All Grade lab abnormalities occurring at a frequency less than 20% included decreased neutrophils.] | 15 | 10 | 44 | 36
Chemistry
Sodium decreased | 57 | 8 | 38 | 7
Potassium decreased | 41 | 4.8 | 34 | 4
Aspartate amino transferase increased | 40 | 2.8 | 29 | 0.4
Sodium increased | 35 | 0.4 | 27 | 0
Alanine aminotransferase increased | 32 | 2 | 25 | 0.9
Activated Partial Thromboplastin Time (sec) increased | 26 | 1.3 | 16 | 0.9
Creatinine increased | 23 | 0.8 | 19 | 0.4
Alkaline phosphate increased | 22 | 0.4 | 26 | 1.4
Magnesium decreased | 21 | 0.8 | 15 | 1.8
Potassium increased | 21 | 0.8 | 12 | 1.8
Creatine Phosphokinase increased | 21 | 1.7 | 11 | 0

DeLLphi-300 and DeLLphi-301

The safety of IMDELLTRA, as a single agent, at the recommended dosage was evaluated in patients with extensive stage small cell lung cancer enrolled in DeLLphi-300 and DeLLphi-301 [see Clinical Studies (14.1)]. Among 187 patients who received IMDELLTRA, 31% were exposed for 6 months or longer and 14% were exposed for greater than one year.

The demographic characteristics of patients who received IMDELLTRA were: median age 66 years (range: 35 to 82); 65% male; 70% White, 26% Asian, 2.1% Black or African American; and 2.1% Hispanic or Latino.

Serious adverse reactions occurred in 58% of patients who received IMDELLTRA. Serious adverse reactions in >3% of patients included cytokine release syndrome (24%), pneumonia (6%), pyrexia (3.7%) and hyponatremia (3.6%). Fatal adverse reactions occurred in 2.7% of patients who received IMDELLTRA including pneumonia 0.5%, aspiration (0.5%), pulmonary embolism (0.5%), respiratory acidosis (0.5%), and respiratory failure (0.5%).

Permanent discontinuation of IMDELLTRA due to an adverse reaction occurred in 7% of patients. Adverse reactions which resulted in permanent discontinuation of IMDELLTRA in >1% of patients included cytokine release syndrome (1.6%) and tumor lysis syndrome (1.1%).

Dosage interruptions of IMDELLTRA due to an adverse reaction occurred in 27% of patients. Adverse reactions which required dosage interruption in ≥ 2% of patients included fatigue (3.2%), cytokine release syndrome (2 .7%) and respiratory tract infection (2.1%).

Table 15 summarizes adverse reactions observed in DeLLphi-300 and DeLLphi-301.

Table 15. Adverse Reactions (≥ 15%) in Patients with ES-SCLC Who Received IMDELLTRA in DeLLphi-300 and DeLLphi-301
Adverse Reaction | IMDELLTRA [Graded using CTCAE Version 4.0 and Version 5.0.] (N = 187)
Adverse Reaction | Any Grade (%) | Grade 3 or 4 (%)
Immune system disorders
Cytokine release syndrome [Based on American Society for Transplantation and Cellular Therapy (ASTCT) 2019.] | 55 | 1.6
General disorders and administration site conditions
Fatigue [Includes fatigue and asthenia.] | 51 | 10
Pyrexia | 36 | 0
Nervous system disorders
Dysgeusia | 36 | 0
Metabolism and nutrition disorders
Decreased appetite | 34 | 2.7
Nausea | 22 | 1.6
Gastrointestinal disorders
Constipation | 30 | 0.5
Musculoskeletal and connective tissue disorders
Musculoskeletal pain [Includes myalgia, arthralgia, back pain, pain in extremity, neck pain, musculoskeletal chest pain, non- cardiac chest pain and bone pain.] | 30 | 1.1
Respiratory, thoracic and mediastinal disorders
Dyspnea [Includes dyspnea and exertional dyspnea.] | 17 | 2.1
Cough | 17 | 0

Table 16 summarizes laboratory abnormalities in DeLLphi-300 and DeLLphi-301
 | IMDELLTRA [The denominator used to calculate the rate varied from 41 to 187 based on the number of patients with a baseline value and at least one post-treatment value.]
 | All Grades (%) | Grade 3 or 4 (%)
Laboratory Abnormality
Hematology
Lymphocytes decreased | 84 | 57
Hemoglobin decreased | 58 | 5
White blood cells decreased | 44 | 3.8
Platelets decreased | 33 | 3.2
Neutrophils decreased [All Grade lab abnormalities occurring at a frequency less than 20% included decreased neutrophils.] | 12 | 6
Chemistry
Sodium decreased | 68 | 16
Potassium decreased | 50 | 5
Aspartate amino transferase increased | 44 | 3.2
Alanine aminotransferase increased | 42 | 2.1
Magnesium decreased | 33 | 1.6
Creatinine increased | 29 | 0.5
Sodium increased | 26 | 0
Alkaline phosphate increased | 22 | 0

8 USE IN SPECIFIC POPULATIONS

8.1 Pregnancy

Risk Summary

Based on its mechanism of action, IMDELLTRA may cause fetal harm when administered to a pregnant woman [see Clinical Pharmacology (12.1)]. There are no available data on the use of IMDELLTRA in pregnant women to inform a drug-associated risk.

In an animal reproduction study, a murine surrogate molecule administered intravenously to pregnant mice crossed the placental barrier.

Tarlatamab-dlle causes T-cell activation and cytokine release; immune activation may compromise pregnancy maintenance.

Human immunoglobulin G (IgG) and proteins comprising IgG-derived fragment crystallizable (Fc) domains are known to cross the placental barrier; therefore, IMDELLTRA has the potential to be transmitted from the mother to the developing fetus. Advise women of the potential risk to the fetus.

In the U.S. general population, the estimated background risk of major birth defects and miscarriage in clinically recognized pregnancies is 2% - 4% and 15% - 20%, respectively.

Data

Animal Data

Animal reproduction studies have not been conducted with tarlatamab-dlle. In an embryo-fetal developmental toxicity study, a murine surrogate molecule was administered intravenously to pregnant mice during the period of organogenesis. The surrogate molecule crossed the placental barrier and did not cause maternal toxicity, embryo-fetal toxicity or teratogenicity.

8.2 Lactation

Risk Summary

There are no data on the presence of tarlatamab-dlle in human milk or the effects on the breastfed child or on milk production. Maternal IgG is known to be present in human milk. The effects of local gastrointestinal exposure and limited systemic exposure in the breastfed child to IMDELLTRA are unknown. Because of the potential for serious adverse reactions in a breastfed child, advise patients not to breastfeed during treatment with IMDELLTRA and for 2 months after the last dose.

8.3 Females and Males of Reproductive Potential

IMDELLTRA may cause fetal harm when administered to a pregnant woman [see Use in Specific Populations (8.1)].

Pregnancy Testing

Verify pregnancy status of females of reproductive potential prior to initiating IMDELLTRA.

Contraception

Females

Advise females of reproductive potential to use effective contraception during treatment with IMDELLTRA and for 2 months after the last dose.

8.4 Pediatric Use

The safety and effectiveness of IMDELLTRA have not been established in pediatric patients.

8.5 Geriatric Use

Of the 473 patients with SCLC who received IMDELLTRA 10 mg as a single agent, 51% were 65 years of age or older and 11% were 75 years of age or older. No overall differences in IMDELLTRA pharmacokinetics, safety or efficacy were observed between older patients (≥ 65 years of age) and younger patients.

11 DESCRIPTION

Tarlatamab-dlle is a bispecific DLL3-directed CD3 T-cell engager that binds to DLL3 expressed on the surface of cells, including tumor cells, and CD3 expressed on the surface of T cells. Tarlatamab-dlle is produced using recombinant DNA technology in Chinese hamster ovary cells. It consists of 982 amino acids and has a molecular weight of approximately 105 kilodaltons.

IMDELLTRA (tarlatamab-dlle) for injection is supplied as a sterile, preservative-free, white to slightly yellow, lyophilized powder in a single-dose vial for reconstitution and further dilution.

Each 1 mg vial contains tarlatamab-dlle (1 mg), glutamic acid (0.72 mg), polysorbate 80 (0.04 mg), sucrose (37.1 mg), and sodium hydroxide to adjust pH to 4.2. After reconstitution with 1.3 mL of Sterile Water for Injection the resulting concentration is 0.9 mg/mL IMDELLTRA.

Each 10 mg vial contains tarlatamab-dlle (10 mg), glutamic acid (3.7 mg), polysorbate 80 (0.2 mg), sucrose (194.4 mg), and sodium hydroxide to adjust pH to 4.2. After reconstitution with 4.4 mL of Sterile Water for Injection the resulting concentration is 2.4 mg/mL IMDELLTRA.

IV Solution Stabilizer is supplied as a sterile, preservative-free, colorless to slightly yellow, clear solution. Each vial of IV Solution Stabilizer contains citric acid monohydrate (36.75 mg), lysine hydrochloride (1598.8 mg), polysorbate 80 (7 mg), sodium hydroxide to adjust pH to 7.0, and water for injection.

12 CLINICAL PHARMACOLOGY

12.1 Mechanism of Action

Tarlatamab-dlle is a bispecific T-cell engager that binds to DLL3 expressed on the surface of cells, including tumor cells, and CD3 expressed on the surface of T cells. Tarlatamab-dlle causes T-cell activation, release of inflammatory cytokines, and lysis of DLL3-expressing cells. Tarlatamab-dlle had anti-tumor activity in mouse models of SCLC.

12.2 Pharmacodynamics

Exposure-Response Relationships

There are no clinically significant exposure-response relationships for efficacy over the exposure range observed between tarlatamab-dlle 10 mg and 100 mg (10 times the highest approved recommended dosage).

There is an exposure-response relationship between tarlatamab-dlle exposure and neutropenia or neurologic toxicity including ICANS with a higher risk of any grade neutropenia or neurologic toxicity including ICANS at higher exposure.

Serum Cytokines

Transient elevation of serum cytokines IL-2, IL-6, IL-8, IL-10, and IFN-γ were observed at a tarlatamab-dlle dosage of 0.3 mg and above. Peak elevation of cytokines was generally observed 24 hours following the initial dose of IMDELLTRA at 1 mg on Cycle 1 Day 1 and generally returned to baseline levels prior to the next infusion on Cycle 1 Day 8.

12.3 Pharmacokinetics

Tarlatamab-dlle pharmacokinetic data in patients with SCLC at the approved recommended dosage are presented as mean (CV%) unless otherwise specified. The exposure of tarlatamab-dlle increases in a dose proportional manner over the dosage range of 1 mg to 100 mg (10 times the highest approved recommended dosage) every 2 weeks. Tarlatamab-dlle steady state is achieved by Cycle 2 Day 15. Pharmacokinetic parameters are summarized for the recommended dosage of IMDELLTRA in Table 17.

Table 17. Pharmacokinetic Parameters of Tarlatamab-dlle
 | Parameter
 | Cavg (ng/mL) | Cmax (ng/mL) | Ctrough (ng/mL)
First step-up dose 1 mg | 106 (26%) | 314 (35%) | 49 (35%)
First treatment dose 10 mg | 1,100 (26%) | 3,190 (35%) | 517 (36%)
Steady state 10 mg every 2 weeks | 1,040 (37%) | 3,640 (35%) | 472 (62%)

Distribution

Tarlatamab-dlle steady state volume of distribution is 8.5 L (33%).

Metabolism

Tarlatamab-dlle is expected to be metabolized into small peptides by catabolic pathways.

Elimination

Tarlatamab-dlle terminal elimination half-life is 11 days (31%) with an estimated systemic clearance of 0.7 L/day (34%).

Specific Populations

No clinically significant differences in the pharmacokinetics of tarlatamab-dlle were observed based on age (20 to 86 years), body weight (35 to 149 kg), sex, race (68% White and 27% Asian), mild or moderate renal impairment (eGFR 30 to < 90 mL/min), or mild hepatic impairment (total bilirubin ≤ upper limit of normal (ULN) and AST > ULN).

The effects of severe renal impairment (eGFR 15 to < 30 mL/min), end-stage renal disease (eGFR <15 mL/min), or moderate to severe hepatic impairment (total bilirubin > 1.5 × ULN and any AST) on the pharmacokinetics of tarlatamab-dlle are unknown.

Effects of Tarlatamab-dlle on CYP450 Substrates

Tarlatamab-dlle causes transient release of cytokines that may suppress CYP450 enzymes and may result in an increased exposure of concomitant CYP substrates during and up to 14 days after occurrence of cytokine release syndrome [see Clinical Pharmacology (12.2)].

12.6 Immunogenicity

The observed incidence of anti-drug antibodies (ADA) is highly dependent on the sensitivity and specificity of the assay. Differences in assay methods preclude meaningful comparisons of the incidence of ADA in the studies described below with the incidence of ADA in other studies, including those of tarlatamab-dlle or of other tarlatamab products.

During the maximum 3-year treatment period during which the presence of ADA was evaluated in DeLLphi-300, DeLLphi-301, and DeLLphi-304, 8% (36/445) of patients who received the recommended step-up and full dose of IMDELLTRA developed treatment- emergent ADA. In DeLLphi-301 and DeLLphi-304, which included neutralizing antibody assessments, 38% (11/29) of the patients who developed treatment-emergent ADA also developed neutralizing antibodies. ADA resulted in a 14% increase in the clearance of tarlatamab-dlle. Because of the low occurrence of ADA, the effect of these antibodies on the pharmacokinetics, pharmacodynamics, safety, and effectiveness of tarlatamab-dlle is unknown.

13 NONCLINICAL TOXICOLOGY

13.1 Carcinogenesis, Mutagenesis, Impairment of Fertility

No carcinogenicity or genotoxicity studies have been conducted with tarlatamab-dlle.

No studies have been conducted to evaluate the effects of tarlatamab-dlle on fertility.

14 CLINICAL STUDIES

14.1 Small Cell Lung Cancer

DeLLphi-304

The efficacy of IMDELLTRA was evaluated in DeLLphi-304 (NCT05740566), a multicenter, randomized, open-label trial. Eligible patients were required to have SCLC with disease progression following treatment with platinum-based chemotherapy with or without an anti-PD-(L)1 antibody. Patients were required to have an ECOG Performance Status of 0 or 1 and at least one measurable lesion per Response Evaluation Criteria in Solid Tumors (RECIST v1.1). Patients with symptomatic brain metastases or active immunodeficiency were ineligible.

A total of 509 patients were randomized 1:1 to receive either IMDELLTRA (N=254) at an initial dose of 1 mg on Cycle 1 Day 1 followed by 10 mg on Days 8, 15, and every 2 weeks thereafter until disease progression or unacceptable toxicity or Investigator's choice of standard of care (SOC) chemotherapy (N=255) (topotecan [73%], lurbinectedin [18%] or amrubicin [9%]) until unacceptable toxicity or disease progression. Randomization was stratified by prior anti-PD-(L)1 exposure (yes versus no), platinum sensitivity status (chemotherapy-free interval (CFI) ≥ 180 days, < 180 to ≥ 90 days, or < 90 days), presence (previous or current) of brain metastases (yes versus no) and investigator's choice of standard of care (topotecan/amrubicin versus lurbinectedin).

The median age was 65 years (range: 20 to 86); 52% age 65 or older; 69% male; 57% White, 40% Asian, 1.4% were other races or had race not reported, 1% Black or African American, 0.4% American Indian or Alaska Native; 32% had ECOG PS of 0 and 67% ECOG PS of 1; 100% had extensive stage disease at baseline of whom 91% had metastatic disease; 45% had brain metastases at baseline; 35% had liver metastases at baseline. Sixty-nine percent (69%) of patients were former smokers, 21% were current smokers, 11% were never smokers. All patients received prior platinum therapy; 71% received prior anti-PD-(L)1 therapy; 223 patients (44%) had chemotherapy-free interval < 90 days after end of first line platinum therapy, while 286 patients (56%) had chemotherapy-free interval ≥ 90 days.

The major efficacy outcome measure was overall survival (OS). Key secondary efficacy outcome measures included progression-free survival (PFS) based on investigator assessment per Response Evaluation Criteria in Solid Tumors Version 1.1 (RECIST 1.1) and select patient reported outcomes.

Efficacy results are summarized in Table 18 and Figure 1.

Table 18. Efficacy Results for Patients with SCLC who received IMDELLTRA
Efficacy Parameter | IMDELLTRA (N = 254) | Standard of Care (N = 255)
Overall Survival (OS)
Deaths (%) | 111 (43.7) | 152 (59.6)
Median [per Kaplan-Meier estimates] in months (95% CI) | 13.6 (11.1, NE) | 8.3 (7.0, 10.2)
Hazard ratio [Hazard ratio based on the stratified Cox proportional hazard model] (95% CI) | 0.60 (0.47, 0.77)
p-value [p-value based on the stratified log-rank test] | <0.001
Progression-free Survival (PFS) [PFS based on investigator assessment per RECIST 1.1]
Events (%) | 191 (75.2) | 205 (80.4)
Median in months (95% CI) | 4.2 (3.0, 4.4) | 3.2 (2.9, 4.2)
Hazard ratio (95% CI) | 0.72 (0.59, 0.88)
p-value | <0.001

In a pre-specified exploratory subgroup analysis, the HR for OS was similar between patients with a chemotherapy-free interval (CFI) <90 days (n=223) and patients with a CFI ≥90 days (n=286), with HRs of 0.60 (95% CI: 0.43, 0.84) and 0.65 (95% CI: 0.45, 0.93), respectively.

Figure 1: Kaplan-Meier Plot of Overall Survival in ITT on DeLLphi-304

The analysis of mean change from baseline in dyspnea as assessed using the EORTC QLQ-C30 and EORTC QLQ-LC13 at week 18 demonstrated a statistically significant improvement in patients randomized to IMDELLTRA compared to SOC. At week 18, 149 patients (59%) randomized to IMDELLTRA and 116 (45%) patients randomized to SOC were still on treatment, and the compliance rates were 79% and 76% respectively at that timepoint.

Figure 2 shows the change from baseline in dyspnea at week 18 in patients who had a change from baseline score at week 18 (n=116 for IMDELLTRA, n=88 for SOC). Two patients with a missing baseline value, both from the IMDELLTRA arm, are not included in the waterfall plot. Patients with no change in dyspnea score are not graphically represented in Figure 2 (n=38 for IMDELLTRA, n=26 for SOC).

Figure 2: Waterfall plot of Change From Baseline in Dyspnea (Composite Score) at Week 18

DeLLphi-301

The efficacy of IMDELLTRA was evaluated in DeLLphi-301 [NCT05060016], an open- label, multicenter, multi-cohort clinical trial. Eligible patients were required to have relapsed/refractory SCLC with disease progression after receiving previous treatment with platinum-based chemotherapy and at least one other line of prior therapy, an ECOG Performance Status of 0 or 1, and at least one measurable lesion as defined by Response Evaluation Criteria in Solid Tumors (RECIST v1.1). The trial excluded patients with symptomatic brain metastases, evidence of interstitial lung disease or non-infectious pneumonitis, and active immunodeficiency.

A total of 99 patients received IMDELLTRA intravenously at an initial dose of 1 mg on Cycle 1 Day 1 followed by 10 mg on Days 8, 15, and every 2 weeks thereafter until disease progression or unacceptable toxicity.

The study population characteristics were: median age 64 years (range: 35 to 82); 48% of patients ≥ 65 years and 10% of patients ≥ 75 years; 72% male; 58% White, 41% Asian; 1% Hispanic or Latino; and 74% have ECOG 1.

Ninety-seven percent of patients had metastatic disease at baseline; 22% had brain metastases at baseline; and 92% were former/current smokers. All patients received prior platinum-based chemotherapy (median two lines); 74% received prior anti-PD-(L)1 therapy (including 59% who received anti-PD[L]1 therapy in combination with platinum-based chemotherapy in the frontline setting); 51% received prior topoisomerase I inhibitor (including 20% who received topotecan). Platinum sensitivity status, defined by time to progression after first line platinum therapy, was known for 69/99 patients. Twenty-seven patients (27%) had platinum-resistant SCLC, defined as time to progression < 90 days after first line platinum therapy, while 42 patients (42%) had platinum-sensitive SCLC.

Tumor assessments were performed every 6 weeks for the first 48 weeks and every 12 weeks thereafter. The major efficacy outcome measures were overall response rate (ORR) and duration of response (DOR) as evaluated by Blinded Independent Central Review (BICR) according to RECIST v1.1.

Efficacy results are presented in Table 19.

Table 19. Efficacy Results for DeLLphi-301
Efficacy Parameter | IMDELLTRA (N = 99)
Overall Response Rate (ORR)
ORR, % (95% CI) [Assessed by Blinded Independent Central Review, CI = Confidence Interval] | 40 (31, 51)
Complete Response, n (%) | 2 (2)
Partial Response, n (%) | 38 (38)
Duration of Response (DOR)
Median [Median based on Kaplan-Meier estimate.] , months (range) | 9.7 (2.7, 20.7+)
Duration ≥ 6 months [Based on observed duration of response.] , % | 68
Duration ≥ 12 months, % | 40

Of the 69 patients with available data regarding platinum sensitivity status, the ORR was 52% (95% CI: 32, 71) in 27 patients with platinum-resistant SCLC and 31% (95% CI: 18, 47) in 42 patients with platinum-sensitive SCLC.

16 HOW SUPPLIED/STORAGE AND HANDLING

16.1 How Supplied

IMDELLTRA (tarlatamab-dlle) for injection is a sterile, preservative-free, white to slightly yellow, lyophilized powder supplied as follows:

- 1 mg package (NDC 55513-059-01) contains 1 single-dose vial of 1 mg IMDELLTRA and 2 vials of 7 mL IV Solution Stabilizer.
- 10 mg package (NDC 55513-077-01) contains 1 single-dose vial of 10 mg IMDELLTRA and 2 vials of 7 mL IV Solution Stabilizer.

16.2 Storage and Handling

Store IMDELLTRA and IV Solution Stabilizer (IVSS) vials refrigerated at 2°C to 8°C (36°F to 46°F) in the original carton to protect from light until time of use. Do not freeze.

IMDELLTRA and IV Solution Stabilizer (IVSS) vials may be kept at room temperature between 20°C to 25°C (68°F to 77°F) for up to 24 hours in the original carton to protect from light.

17 PATIENT COUNSELING INFORMATION

Advise the patient to read the FDA-approved patient labeling (Patient Information).

Cytokine Release Syndrome (CRS)

Inform patients and their caregivers of the risk of CRS, and to immediately contact their healthcare provider for signs and symptoms associated with CRS including pyrexia, hypotension, fatigue, tachycardia, headache, hypoxia, nausea and vomiting [see Warnings and Precautions (5.1)].

Advise patients that they should be monitored from the start of the IMDELLTRA infusion for 22 to 24 hours on Cycle 1 Day 1 and Cycle 1 Day 8 doses in an appropriate healthcare setting [see Warnings and Precautions (5.1)].

Advise patients to remain within 1 hour of an appropriate healthcare setting for a total of 48 hours from start of the infusion with IMDELLTRA following Cycle 1 Day 1 and Cycle 1 Day 8 doses, accompanied by a caregiver.

Neurologic Toxicity Including Immune Effector Cell Associated Neurotoxicity Syndrome (ICANS)

Discuss the signs and symptoms associated with ICANS with patients and their caregivers. Advise patients to immediately contact their healthcare provider if they experience any signs or symptoms of ICANS, such as encephalopathy, confusion, delirium, seizure, ataxia, weakness or numbness of arms and legs, tremor, and headache.

Advise patients who experience neurologic toxicity or symptoms of ICANS to refrain from driving, operating heavy or potentially dangerous machinery, and engaging in hazardous occupations or activities during treatment with IMDELLTRA [see Warnings and Precautions (5.2)].

Cytopenias

Discuss the signs and symptoms associated with cytopenias, including neutropenia and febrile neutropenia, anemia, and thrombocytopenia with patients and their caregivers [see Warnings and Precautions (5.3)]. Inform patients that they will need to undergo lab tests to monitor blood counts. Advise patients to immediately contact their healthcare provider if they experience any signs or symptoms of cytopenias.

Infections

Discuss the signs and symptoms of infections with patients and their caregivers. Advise patients of the risk of serious infections, and to immediately contact their healthcare provider for signs or symptoms of infections [see Warnings and Precautions (5.4)].

Hepatotoxicity

Discuss the signs and symptoms of hepatotoxicity and bilirubin with patients and their caregivers. Inform patients that they will need to undergo lab tests to monitor liver function. Advise patients to immediately contact their healthcare provider for signs and symptoms of liver dysfunction [see Warnings and Precautions (5.5)].

Hypersensitivity

Discuss the signs and symptoms of allergic reactions with patients and their caregivers. Advise patients to immediately seek medical attention for any signs and symptoms of severe reactions [see Warnings and Precautions (5.6)].

Embryo-Fetal Toxicity

Advise pregnant women and females of reproductive potential of the potential risk to a fetus. Advise females of reproductive potential to inform their healthcare provider if they are pregnant or become pregnant. Advise females of reproductive potential to use effective contraception during treatment with IMDELLTRA and for 2 months after the last dose [see Warnings and Precautions (5.7), Use in Specific Populations (8.1, 8.3)].

Lactation

Advise women not to breastfeed during treatment with IMDELLTRA and for 2 months after the last dose [see Use in Specific Populations (8.2)].

IMDELLTRA® (tarlatamab-dlle)

Manufactured by:
Amgen Inc.
One Amgen Center Drive
Thousand Oaks, CA 91320-1799 U.S.A.
U.S. License No. 1080
Patent: http://pat.amgen.com/imdelltra/

© 2024 - 2025 Amgen Inc. All rights reserved.

1XXXXXX – V2

MEDICATION GUIDE
IMDELLTRA® (im del trah) (tarlatamab-dlle)
for injection, for intravenous use

What is the most important information I should know about IMDELLTRA?
IMDELLTRA can cause serious side effects, including:

- Cytokine Release Syndrome (CRS). CRS is common during treatment with IMDELLTRA and can also be severe, life-threatening, or cause death. Tell your healthcare provider or get medical help right away if you develop any signs or symptoms of CRS, including:

- fever of 100.4°F (38°C) or higher
- low blood pressure
- tiredness
- fast heartbeat or dizziness
- headache
- shortness of breath or trouble breathing

- nausea and vomiting
- confusion, restlessness, or feeling anxious
- problems with balance and movement, such as trouble walking
- heart, liver, or kidney problems
- blood clots or unusual bleeding or bleeding that lasts a long time

Due to the risk of CRS, you will receive IMDELLTRA on a "step-up dosing schedule":

- The step-up dosing schedule is when you receive a smaller dose of IMDELLTRA on Day 1 of your first treatment cycle (Cycle 1).
- You will receive the full treatment dose of IMDELLTRA on Day 8 and Day 15 of Cycle 1. You will receive the full treatment dose 1 time every 2 weeks after Day 15 of Cycle 1.
- If your dose of IMDELLTRA is delayed for any reason, you may need to repeat the step-up dosing schedule.
- Before receiving your Day 1 and Day 8 doses of Cycle 1 of IMDELLTRA, you will be given a medicine to help reduce your risk of CRS. This will be given into your vein by intravenous (IV) infusion. You will also receive IV fluids after each of your Cycle 1 Day 1 and Day 8 doses. Your healthcare provider will decide if you need to receive medicines to help reduce your risk of CRS with future doses.
- See "How will I receive IMDELLTRA?" for more information about how you will receive IMDELLTRA.

- Neurologic Problems. IMDELLTRA can cause neurologic problems that can be severe, life-threatening, or cause death. Neurologic problems may happen days or weeks after you receive IMDELLTRA. Your healthcare provider may refer you to a healthcare provider who specializes in neurologic problems. Tell your healthcare provider right away if you develop any signs or symptoms of neurologic problems, including:

- changes in taste
- headache
- numbness or tingling of your hands or feet
- dizziness
- trouble sleeping
- muscle weakness or numbness of arms or legs
- problems with walking, or loss of balance or coordination

- trouble speaking, memory loss, or personality changes
- confusion, feeling disoriented, slow thinking, or not being able to think clearly
- fainting or loss of consciousness
- seizures
- shaking (tremors)
- sleepiness
- feeling like you have no energy

Due to the risk of CRS and neurologic problems you will receive the following monitoring during treatment with IMDELLTRA:

- For Day 1 and Day 8 of Cycle 1 doses, your healthcare provider will monitor you for 22 to 24 hours from the start of the IMDELLTRA infusion in an appropriate healthcare setting that can manage these side effects.
- You should remain within 1 hour of an appropriate healthcare setting for a total of 48 hours from the start of the IMDELLTRA infusion after your Day 1 and Day 8 of Cycle 1 doses and be accompanied by a caregiver.
- For Day 15 of Cycle 1 and Cycle 2 doses, your healthcare provider will watch you for 6 to 8 hours after the IMDELLTRA infusion.
- For Cycle 3 and Cycle 4 doses, your healthcare provider will watch you for 3 to 4 hours after the IMDELLTRA infusion.
- For Cycle 5 and later doses, your healthcare provider will watch you for 2 hours after the IMDELLTRA infusion.

Your healthcare provider will monitor you for signs and symptoms of CRS and neurologic problems during treatment with IMDELLTRA and treat you as needed. You may be hospitalized if you develop signs or symptoms of CRS or neurologic problems during treatment with IMDELLTRA. Your healthcare provider may temporarily stop or completely stop your treatment with IMDELLTRA if you develop CRS or neurologic problems.
See "What are the possible side effects of IMDELLTRA?" for more information about side effects.

What is IMDELLTRA?
IMDELLTRA is a prescription medicine used to treat adults with extensive stage small cell lung cancer (ES-SCLC), which is cancer that has spread throughout the lung or to other parts of the body, and who have received treatment with chemotherapy that contains platinum, and it did not work or is no longer working.
It is not known if IMDELLTRA is safe and effective in children.

Before receiving IMDELLTRA, tell your healthcare provider about all of your medical conditions, including if you:

- have an infection
- are pregnant or plan to become pregnant. IMDELLTRA may harm your unborn baby.
  Females who are able to become pregnant:
  - Your healthcare provider should do a pregnancy test before you start treatment with IMDELLTRA.
  - You should use an effective form of birth control (contraception) during treatment with IMDELLTRA, and for 2 months after your last dose of IMDELLTRA.
  - Tell your healthcare provider right away if you become pregnant or think that you may be pregnant during treatment with IMDELLTRA.
- are breastfeeding or plan to breastfeed. It is not known if IMDELLTRA passes into your breast milk. Do not breastfeed during treatment with IMDELLTRA and for 2 months after the last dose of IMDELLTRA.

Tell your healthcare provider about all the medicines you take, including prescription and over-the-counter medicines, vitamins, and herbal supplements.

How will I receive IMDELLTRA?

- IMDELLTRA will be given to you by your healthcare provider by intravenous (IV) infusion through a needle placed in a vein. The infusion will take about 1 hour.
- Your IMDELLTRA treatment schedule is divided into cycles that are usually 28 days (4 weeks) long.
- Your healthcare provider will decide how many treatment cycles you will receive.
- See "What is the most important information I should know about IMDELLTRA?" for more information about how you will receive IMDELLTRA.

What should I avoid while receiving IMDELLTRA?
Do not drive, operate heavy or potentially dangerous machinery or do other dangerous activities, including work-related activities, during treatment with IMDELLTRA if you develop dizziness, confusion, tremors, sleepiness, or any other symptoms that impair consciousness until your signs and symptoms go away. These may be signs and symptoms of neurologic problems. See "What is the most important information I should know about IMDELLTRA" for more information about signs and symptoms of neurologic problems.

What are the possible side effects of IMDELLTRA?
IMDELLTRA can cause serious side effects, including:

- See "What is the most important information I should know about IMDELLTRA?"
- Low blood cell counts (cytopenia). Decreased blood cell counts can be severe and may include the following:
  - low white blood cell counts (neutropenia). Low white blood cells can increase your risk for infection.
  - low red blood cell counts (anemia). Low red blood cells can cause tiredness and shortness of breath.
  - low platelet counts (thrombocytopenia). Low platelet counts can cause bruising or bleeding problems.
- Infections. IMDELLTRA can cause serious infections that can be life-threatening and cause death. Your healthcare provider will check you for signs and symptoms of infection before and during treatment with IMDELLTRA. Tell your healthcare provider right away if you develop any signs or symptoms of infection during treatment with IMDELLTRA, including:

- fever of 100.4°F (38°C) or higher
- cough
- chest pain
- tiredness
- shortness of breath

- painful rash
- sore throat or runny nose
- pain during urination
- feeling weak or generally unwell
- yeast infections in the mouth or other areas

- Liver problems. IMDELLTRA can cause increased liver enzymes and bilirubin in your blood. These increases can happen with or without you also having CRS. Tell your healthcare provider right away if you develop any signs or symptoms of liver problems, including:

- tiredness
- loss of appetite
- pain in your right upper stomach-area (abdomen)

- dark urine
- yellowing of your skin or the white part of your eyes

- Allergic reactions. IMDELLTRA can cause allergic reactions that can be severe. Go to the nearest emergency room or get medical help right away if you develop any signs or symptoms of a severe allergic reaction during treatment with IMDELLTRA, including:

- shortness of breath or trouble breathing
- pain or tightness in your chest and back
- wheezing

- coughing
- feeling lightheaded or dizzy
- rash

Your healthcare provider will do bloodwork before you start and during treatment with IMDELLTRA. Your healthcare provider will monitor you for signs or symptoms of these serious side effects during treatment and may temporarily or completely stop treatment with IMDELLTRA if you develop certain serious side effects.
The most common side effects of IMDELLTRA also include:

- tiredness
- decreased appetite
- a bad or metallic taste in your mouth
- fever

- muscle or bone pain
- constipation
- nausea

The most common severe abnormal blood test results with IMDELLTRA include: decreased white blood cells, decreased sodium, and increased uric acid.
These are not all of the possible side effects of IMDELLTRA.
Call your doctor for medical advice about side effects. You may report side effects to FDA at 1-800-FDA-1088.

General information about the safe and effective use of IMDELLTRA
Medicines are sometimes prescribed for purposes other than those listed in a Medication Guide. You can ask your pharmacist or healthcare provider for information about IMDELLTRA that is written for health professionals.

What are the ingredients in IMDELLTRA?
Active ingredients: tarlatamab-dlle
Inactive ingredients: glutamic acid, polysorbate 80, sucrose, and sodium hydroxide.
Inactive ingredients of IV Solution Stabilizer: citric acid monohydrate, lysine hydrochloride, polysorbate 80, sodium hydroxide and water for Injection.
Manufactured by: Amgen Inc., One Amgen Center Drive, Thousand Oaks, CA 91320-1799
U.S. License No. 1080
© 2024-2025 Amgen Inc. All rights reserved. V2
For more information, go to www.imdelltra.com or call Amgen at 1-800-772-6436.

This Medication Guide has been approved by the U.S. Food and Drug Administration.

Revised: 11/2025

PRINCIPAL DISPLAY PANEL - Kit Carton - 1 mg/vial

Contains 1 IMDELLTRA Single-Dose Vial
Contains 2 IV Solution Stabilizer Vials

NDC 55513-059-01

AMGEN

IMDELLTRA®
(tarlatamab-dlle)
for injection

1
mg/vial

1 mg/vial

For Intravenous Infusion after Dilution

Store refrigerated at 2°C to 8°C (36°F to 46°F) in the
original carton to protect from light until time of use.
Do not freeze.
ATTENTION: Dispense the enclosed Medication
Guide to each patient.

Must be reconstituted
with sterile water for
injection and further
diluted.

No Preservative
Single-Dose Vial –
Discard unused portion.

Rx Only

PRINCIPAL DISPLAY PANEL - Kit Carton - 10 mg/vial

Contains 1 IMDELLTRA Single-Dose Vial
Contains 2 IV Solution Stabilizer Vials

NDC 55513-077-01

AMGEN

IMDELLTRA®
(tarlatamab-dlle)
for injection

10
mg/vial

10 mg/vial

For Intravenous Infusion after Dilution

Store refrigerated at 2°C to 8°C (36°F to 46°F) in the
original carton to protect from light until time of use.
Do not freeze.
ATTENTION: Dispense the enclosed Medication
Guide to each patient.

Must be reconstituted
with sterile water for
injection and further
diluted.

No Preservative
Single-Dose Vial –
Discard unused portion.

Rx Only